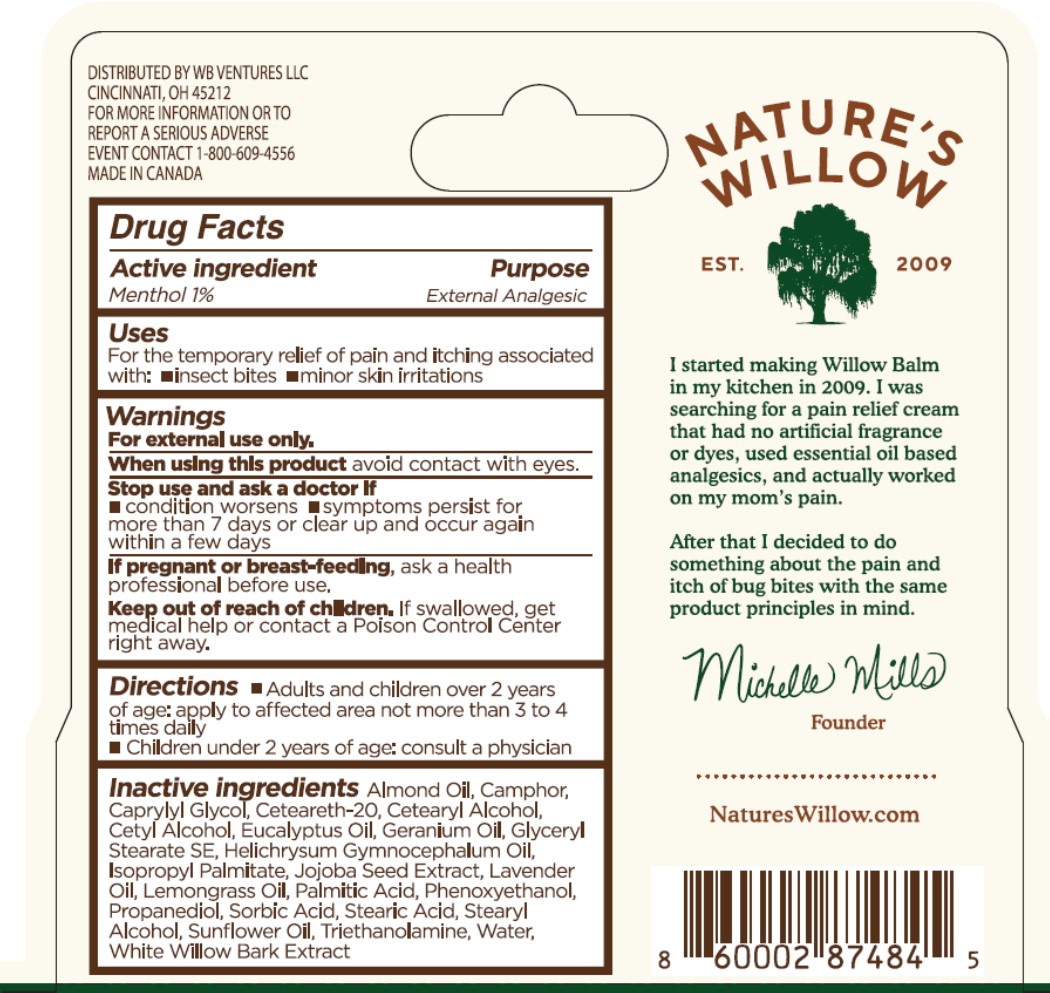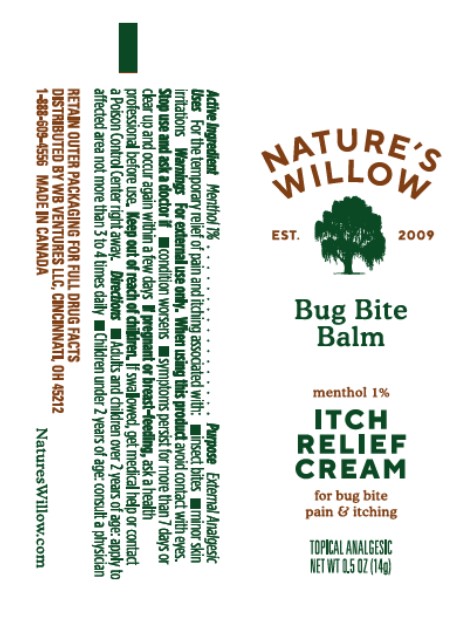 DRUG LABEL: Natures Willow Bug Bite Balm
NDC: 73498-022 | Form: CREAM
Manufacturer: WB Ventures LLC
Category: otc | Type: HUMAN OTC DRUG LABEL
Date: 20231219

ACTIVE INGREDIENTS: MENTHOL 10 mg/1 g
INACTIVE INGREDIENTS: STEARIC ACID; PELARGONIUM GRAVEOLENS FLOWER OIL; GLYCERYL STEARATE SE; PROPANEDIOL; POLYOXYL 20 CETOSTEARYL ETHER; WEST INDIAN LEMONGRASS OIL; SIMMONDSIA CHINENSIS SEED; ISOPROPYL PALMITATE; HELICHRYSUM GYMNOCEPHALUM WHOLE; EUCALYPTUS OIL; CETYL ALCOHOL; CETOSTEARYL ALCOHOL; CAPRYLYL GLYCOL; CAMPHOR (SYNTHETIC); SORBIC ACID; SALIX ALBA BARK; SUNFLOWER OIL; STEARYL ALCOHOL; PHENOXYETHANOL; PALMITIC ACID; LAVENDER OIL; WATER; TROLAMINE; ALMOND OIL

Nature's Willow Bug Bite Balm

SPL Unclassified Section

Drug Facts

Active ingredient

Menthol 1%

Purpose

External Analgesic

Uses

For the temporary relief of pain and itching associated with:

- insect bites

- minor skin irritations

Warnings

For external use only.

When using this product avoid contact with eyes.

Stop use and ask a doctor if

- condition worsens

- symptoms persist for more than 7 days or clear up and occur again within a few days

If pregnant or breast-feeding, ask a health professional before use.

Keep out of reach of children. If swallowed, get medical help or contact a Poison Control Center right away.

Directions

Adults and children over 2 years of age: apply to affected area not more than 3 to 4 times daily

Children under 2 years of age: consult a physician

Inactive ingredients

Almond Oil, Camphor, Caprylyl Glycol, Ceteareth-20, Cetearyl Alcohol, Cetyl Alcohol, Eucalyptus Oil, Geranium Oil, Glyceryl Stearate SE, Helichrysum Gymnocephalum Oil, Isopropyl Palmitate, Jojoba Seed Extract, Lavender Oil, Lemongrass Oil, Palmitic Acid, Phenoxyethanol, Propanediol, Sorbic Acid, Stearic Acid, Stearyl Alcohol, Sunflower Oil, Triethanolamine, Water, White Willow Bark Extract

SPL Unclassified Section

Distributed by WB Ventures LLC, Cincinnati, OH 45212

For more information or to report a serious adverse event contact 1-888-609-4556